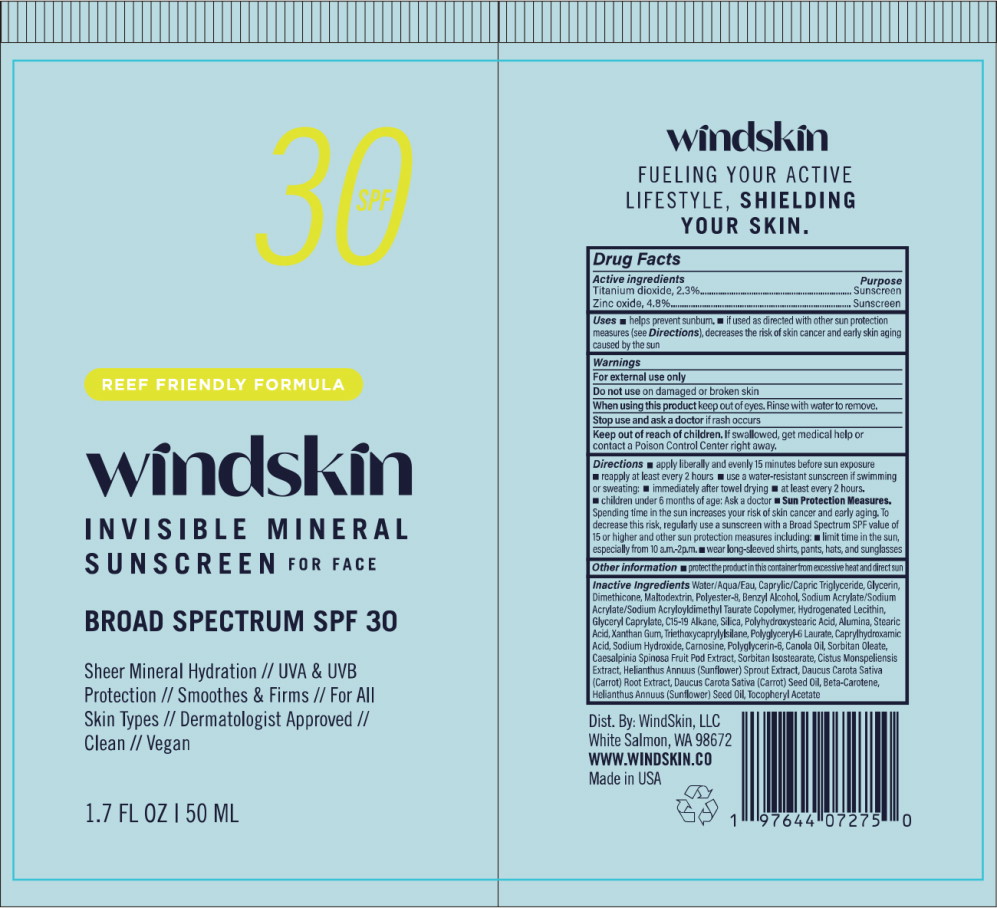 DRUG LABEL: Invisible Mineral Sunscreen for face
NDC: 84290-200 | Form: LOTION
Manufacturer: Windskin LLC
Category: otc | Type: HUMAN OTC DRUG LABEL
Date: 20230628

ACTIVE INGREDIENTS: Zinc Oxide 48 mg/1 mL; Titanium Dioxide 23 mg/1 mL
INACTIVE INGREDIENTS: Water; Medium-Chain Triglycerides; Glycerin; Dimethicone; Maltodextrin; Polyester-8 (1400 MW, CYANODIPHENYLPROPENOYL CAPPED); Benzyl Alcohol; Sodium Acrylate/Sodium Acryloyldimethyltaurate Copolymer (4000000 MW); Hydrogenated Soybean Lecithin; Glyceryl Monocaprylate; C15-19 Alkane; Silicon Dioxide; Polyhydroxystearic Acid (2300 MW); Aluminum Oxide; Stearic Acid; Xanthan Gum; Triethoxycaprylylsilane; Polyglyceryl-6 Laurate; Caprylhydroxamic Acid; Sodium Hydroxide; Caesalpinia Spinosa Fruit Pod; Carnosine; Polyglycerin-6; Canola Oil; Sorbitan Monooleate; Sorbitan Isostearate; Helianthus Annuus Sprout; Cistus Monspeliensis Whole; Carrot; Carrot Seed Oil; Beta Carotene; Sunflower Oil; .Alpha.-Tocopherol Acetate

Drug Facts

Active ingredients

Titanium dioxide, 2.3%

Zinc oxide, 4.8%

Purpose

Sunscreen

Sunscreen

Uses

- helps prevent sunburn.
- if used as directed with other sun protection measures (see Directions), decreases the risk of skin cancer and early skin aging caused by the sun

Warnings

For external use only

Do not use on damaged or broken skin

When using this product keep out of eyes. Rinse with water to remove.

Stop use and ask a doctor if rash occurs

Keep out of reach of children. If swallowed, get medical help or contact a Poison Control Center right away.

Directions

- apply liberally and evenly 15 minutes before sun exposure
- reapply at least every 2 hours
- use a water-resistant sunscreen if swimming or sweating:
  - immediately after towel drying
  - at least every 2 hours.
  - children under 6 months of age: Ask a doctor
- Sun Protection Measures. Spending time in the sun increases your risk of skin cancer and early aging. To decrease this risk, regularly use a sunscreen with a Broad Spectrum SPF value of 15 or higher and other sun protection measures including:
  - limit time in the sun, especially from 10 a.m.-2p.m.
  - wear long-sleeved shirts, pants, hats, and sunglasses

Inactive Ingredients

Water/Aqua/Eau, Caprylic/Capric Triglyceride, Glycerin, Dimethicone, Maltodextrin, Polyester-8, Benzyl Alcohol, Sodium Acrylate/Sodium Acrylate/Sodium Acryloyldimethyl Taurate Copolymer, Hydrogenated Lecithin, Glyceryl Caprylate, C15-19 Alkane, Silica, Polyhydroxystearic Acid, Alumina, Stearic Acid, Xanthan Gum, Triethoxycaprylylsilane, Polyglyceryl-6 Laurate, Caprylhydroxamic Acid, Sodium Hydroxide, Carnosine, Polyglycerin-6, Canola Oil Sorbitan Oleate, Caesalpinia Spinosa Fruit Pod Extract, Sorbitan Isostearate, Cistus Monspeliensis Extract Helianthus Annuus (Sunflower) Sprout Extract, Daucus Carota Sativa (Carrot) Root Extract, Daucus Carota Sativa (Carrot) Seed Oil, Beta-Carotene, Helianthus Annuus (Sunflower) Seed Oil, Tocopheryl Acetate

Dist. By: WindSkin, LLC
White Salmon, WA 98672
WWW.WINDSKIN.CO
Made in USA

Principal Display Panel – 50 mL Tube Label

SPF 30

REEF FRIENDLY FORMULA

windskin

INVISIBLE MINERAL
SUNSCREEN FOR FACE

BROAD SPECTRUM SPF 30

Sheer Mineral Hydration // UVA & UVB
Protection // Smoothes & Firms // For All
Skin Types // Dermatologist Approved //
Clean // Vegan

1.7 FL OZ | 50 ML